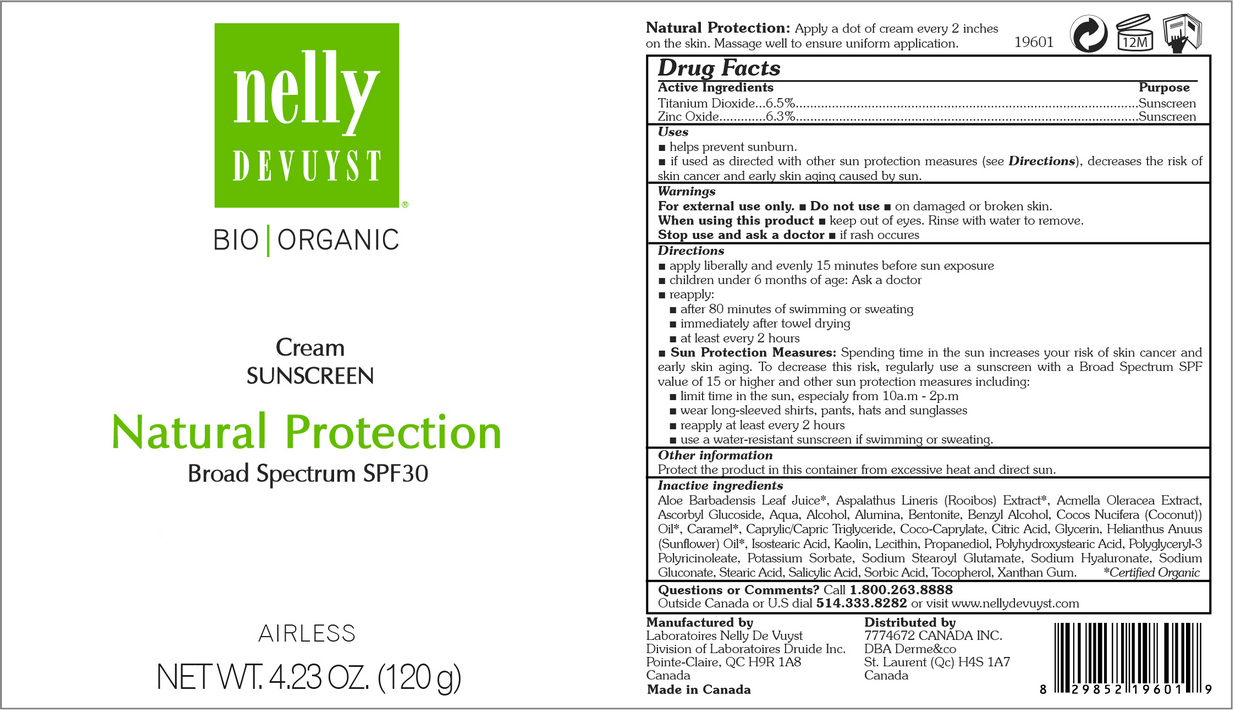 DRUG LABEL: NELLY DEVUYST ORGANIC SUNSCREEN NATURAL PROTECTION BROAD SPECTRUM
NDC: 71447-002 | Form: CREAM
Manufacturer: LABORATOIRES DRUIDE INC
Category: otc | Type: HUMAN OTC DRUG LABEL
Date: 20170605

ACTIVE INGREDIENTS: TITANIUM DIOXIDE 65 g/1 g; ZINC OXIDE 63 g/1 g
INACTIVE INGREDIENTS: SORBIC ACID; TOCOPHEROL; MEDIUM-CHAIN TRIGLYCERIDES; PROPANEDIOL; POTASSIUM SORBATE; SODIUM STEAROYL GLUTAMATE; HYALURONATE SODIUM; SUNFLOWER OIL; ALOE VERA LEAF; ASPALATHUS LINEARIS LEAF; ACMELLA OLERACEA FLOWERING TOP; ALCOHOL; BENTONITE; COCO-CAPRYLATE; ALUMINUM OXIDE; GLYCERIN; STEARIC ACID; XANTHAN GUM; CARAMEL; COCONUT OIL; LECITHIN, SUNFLOWER; POLYHYDROXYSTEARIC ACID (2300 MW); POLYGLYCERIN-3; SODIUM GLUCONATE; SALICYLIC ACID; ASCORBYL GLUCOSIDE; WATER; BENZYL ALCOHOL; ANHYDROUS CITRIC ACID; ISOSTEARIC ACID; KAOLIN

Active Ingredients

Titanium Dioxide 6.5%
Zinc Oxide 6.3%

Purpose

Sunscreen

Uses

▪ Helps prevent sunburn. ▪ If used as directed with other sun protection measures (see Directions), decreases the risk of skin cancer and early skin aging caused by the sun.

Warnings

For external use only

Do not use

on damaged or broken skin.

When using this product

keep out of eyes. Rinse with water to remove.

Stop use and ask a doctor if

rash occurs.

Keep out of reach of children

If swallowed, get medical help or contact Poison Control Center right away.

Directions

▪ Apply liberally and evenly 15 minutes before sun exposure ▪ Reapply ▪ After 80 minutes of swimming or
sweating ▪ Immediately after towel drying ▪ At least every 2 hours ▪ Sun Protection Measures ▪ Spending
time in the sun increases your risk of skin cancer and early skin aging. To decrease this risk, regularly
use a sunscreen with a Broad Spectrum SPF value of 15 or higher and other sun protection measures
including: ▪ Limit time in the sun, especially from 10 a.m. - 2 p.m. ▪ Wear long-sleeved shirts, pants,
hats, and sunglasses ▪ Use a water-resistant sunscreen if swimming or sweating.

Other Information

Protect the product in this container from excessive heat and direct sun.

Inactive Ingredients

ALOE BARBADENSIS LEAF JUICE*, ASPALATHUS LINERIS (ROOIBOS) EXTRACT*, ACMELLA OLERACEA EXTRACT, ASCORBYL GLUCOSIDE, AQUA, ALCOHOL, ALUMINA, BENTONITE, BENZYL ALCOHOL, COCOS NUCIFERA (COCONUT) OIL*, CARAMEL*, CAPRYLIC/CAPRIC TRIGLYCERIDE, COCO-CAPRYLATE, CITRIC ACID, GLYCERIN, HELIANTHUS ANUUS (SUNFLOWER) OIL*, ISOSTEARIC ACID, KAOLIN, LECITHIN, PROPANEDIOL, POLYHYDROXYSTEARIC ACID, POLYGLYCERYL-3 POLYRICINOLEATE, POTASSIUM SORBATE, SODIUM STEAROYL GLUTAMATE, SODIUM HYALURONATE, SODIUM GLUCONATE, STEARIC ACID, SALICYLIC ACID, SORBIC ACID, TOCOPHEROL, XANTHAN GUM.

*Certified Organic .

Questions or Comments?

1-800-263-8888
Outside Canada or the United States dial 514-333-8282 or visit www.nellydevuyst.com